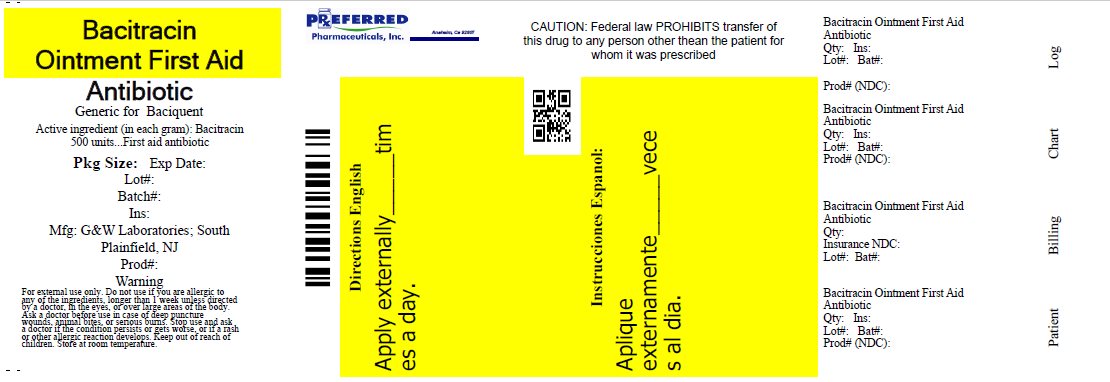 DRUG LABEL: Bacitracin
NDC: 68788-9794 | Form: OINTMENT
Manufacturer: Preferred Pharmaceuticals, Inc
Category: otc | Type: HUMAN OTC DRUG LABEL
Date: 20250106

ACTIVE INGREDIENTS: Bacitracin 500 [USP'U]/1 g
INACTIVE INGREDIENTS: Light Mineral Oil; Petrolatum

Bacitracin Ointment

ACTIVE INGREDIENT

Bacitracin 500 units

PURPOSE

First aid antibiotic

USES

first aid to help prevent infection in minor cuts, scrapes and burns

WARNINGS

For external use only
Do not use
• if you are allergic to any of the ingredients
• in the eyes
• over large areas of the body
• longer than 1 week unless directed by a doctor
Ask a doctor before use in case of deep or puncture wounds, animal bites, or serious burns
Stop use and ask a doctor if
• the condition persists or gets worse
• a rash or other allergic reaction develops

KEEP OUT OF REACH OF CHILDREN

If swallowed, get medical help or contact a Poison Control Center right away.

DIRECTIONS

• clean the affected area
• apply a small amount of this product (an amount equal to the surface area of the tip of a finger) on the area 1 to 3 times daily
• may be covered with a sterile bandage

OTHER INFORMATION

store at room temperature

INACTIVE INGREDIENT

light mineral oil, white petrolatum

HOW SUPPLIED

28gm tube – 68788-9794-2

Relabeled By: Preferred Pharmaceuticals, Inc